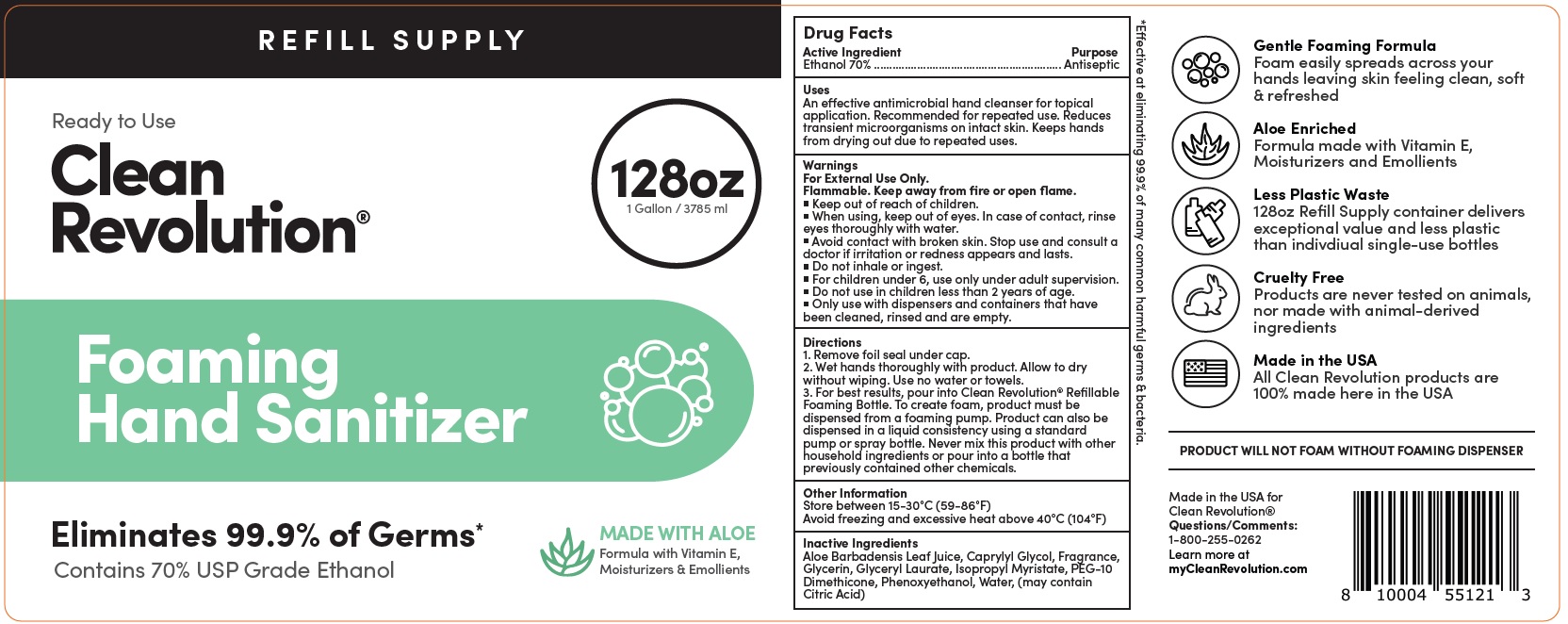 DRUG LABEL: Clean Revolution Foaming Hand Sanitizer Refill Supply Container - Gentle and Aloe Enriched - ELIMINATES 99.9% Germs - 70% Ethanol - Ready To Use
NDC: 74810-725 | Form: LIQUID
Manufacturer: Replenish Bottling LLC
Category: otc | Type: HUMAN OTC DRUG LABEL
Date: 20231226

ACTIVE INGREDIENTS: ALCOHOL 70 mL/100 mL
INACTIVE INGREDIENTS: ALOE VERA LEAF; CAPRYLYL GLYCOL; GLYCERIN; GLYCERYL LAURATE; ISOPROPYL MYRISTATE; PHENOXYETHANOL; WATER

Clean Revolution Foaming Hand Sanitizer Refill Supply Container | Gentle & Aloe Enriched | ELIMINATES 99.9% Germs | 70% Ethanol | Ready To Use

Active Ingredient

Ethanol 70%

Purpose

Antiseptic

Uses

An effective antimicrobial hand cleanser for topical application. Recommended for repeated use. Reduces transient microorganisms on intact skin. Keeps hands from drying out due to repeated uses.

Warnings

For External Use Only.

Flammable. Keep away from fire or open flame.

When using,

- keep out of eyes. In case of contact, rinse eyes thoroughly with water.
- Avoid contact with borken skin.

Stop use and consult a doctor

- if irritation or redness appears and lasts.
- Do not inhale or ingest.
- For children under 6, use only under adult supervision.

Do not use

- in children less than 2 years of age.
- Only use with dispensers and containers that have been cleaned, rinsed and are empty.

Directions

1. Remove foil seal under cap.
2. Wet hands thoroughly with product. Allow to dry without wiping. Use no water or towels.
3. For best results, pour into Clean Revolution® Refillable Foaming Bottle. To create foam, product must be dispensed from a foaming pump. Product can also bedispensed in a liquid consistency using a standard pump or spray bottle. Never mix this product with otherhousehold ingredients or pour into a bottle that previously contained other chemicals.

Other Information

Store between 15-30°C (59-86°F)
Avoid freezing and excessive heat above 40°C (104°F)

Inactive Ingredients

Aloe Barbadensis Leaf Juice, Caprylyl Glycol, Fragrance, Glycerin, Glyceryl Laurate, Isopropyl Myristate, PEG-10 Dimethicone, Phenoxyethanol, Water, (may contain Citric Acid)